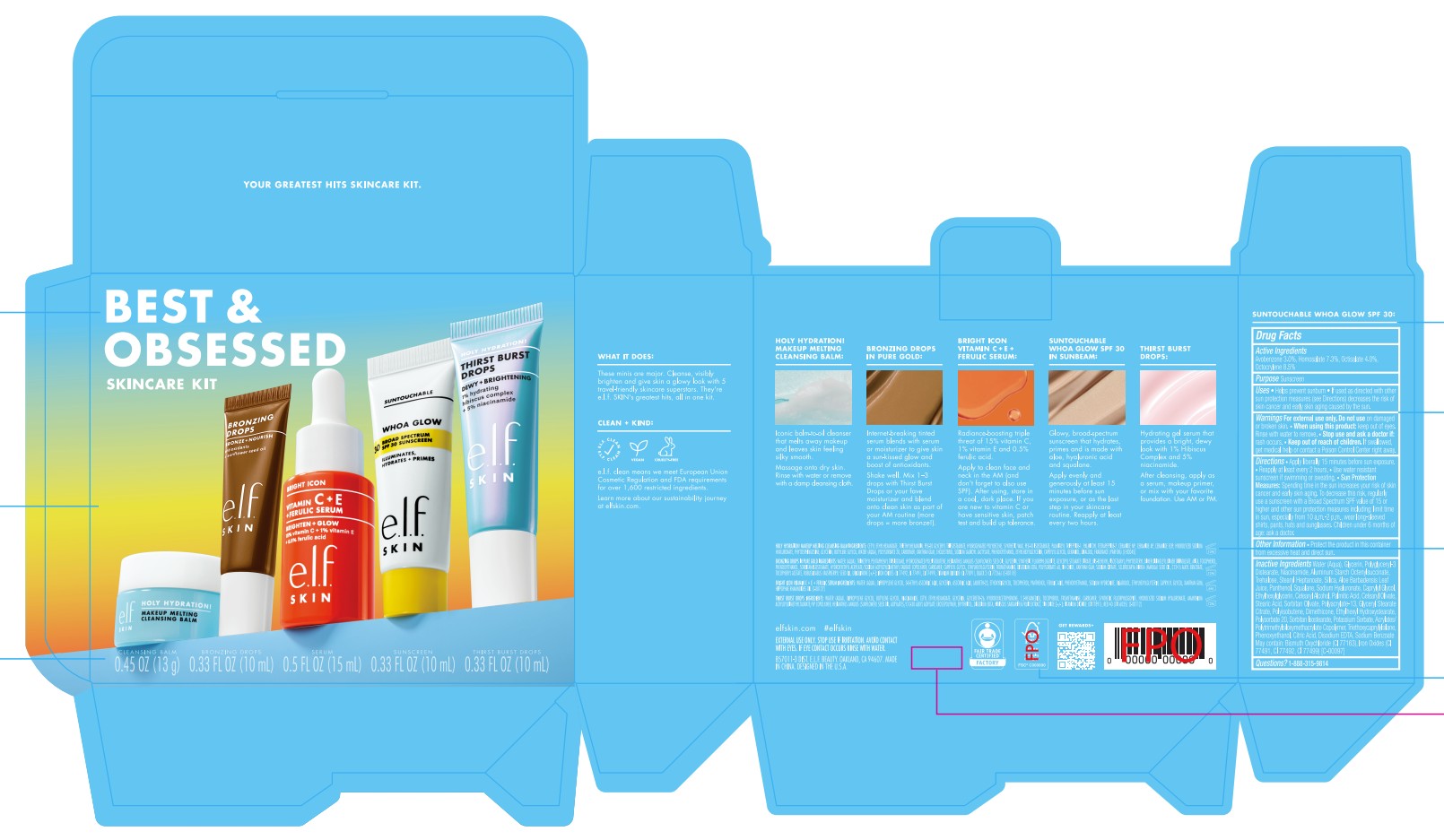 DRUG LABEL: e.l.f. Best and Obsessed Skincare Set
NDC: 76354-484 | Form: KIT | Route: TOPICAL
Manufacturer: e.l.f. Cosmetics, Inc.
Category: otc | Type: HUMAN OTC DRUG LABEL
Date: 20260218

ACTIVE INGREDIENTS: OCTOCRYLENE 85 mg/1 mL; HOMOSALATE 73 mg/1 mL; OCTISALATE 40 mg/1 mL; AVOBENZONE 30 mg/1 mL
INACTIVE INGREDIENTS: POLYACRYLATE-13; NIACINAMIDE; CITRIC ACID; POLYGLYCERYL-3 DISTEARATE; TREHALOSE; POTASSIUM SORBATE; DIMETHICONE; POLYSORBATE 20; SODIUM BENZOATE; BUTYL ACRYLATE/METHYL METHACRYLATE/TRIMETHYLSILOXYMETHACRYLATE COPOLYMER; SILICA; ETHYLHEXYLGLYCERIN; SODIUM HYALURONATE; CAPRYLYL GLYCOL; CETEARYL ALCOHOL; TRIETHOXYCAPRYLYLSILANE; WATER; SQUALANE; CETEARYL OLIVATE; GLYCERYL STEARATE CITRATE; HYDROGENATED POLYISOBUTENE (450 MW); ETHYLHEXYL HYDROXYSTEARATE; CI 77491; STEARIC ACID; SORBITAN OLIVATE; BISMUTH OXYCHLORIDE; CI 77499; PHENOXYETHANOL; CI 77492; PANTHENOL; PALMITIC ACID; ALOE BARBADENSIS LEAF JUICE; GLYCERIN; ALUMINUM STARCH OCTENYLSUCCINATE; STEARYL HEPTANOATE; SORBITAN ISOSTEARATE; EDETATE DISODIUM

e.l.f. Best and Obsessed Skincare Set

Active Ingredients

Avobenzone 3.0%

Homosalate 7.3%

Octisalate 4.0%

Octocrylene 8.5%

Purpose

Sunscreen

Uses

- Helps prevent sunburn.
- If used as directed with other sun protection measures (see Directions) decreases the risk of skin cancer and early skin aging caused by the sun.

Warnings

For external use only.

Do not use

on broken or damaged skin.

When using this product

keep out of eyes. Rinse with water to remove.

Stop use and ask a doctor if:

rash occurs.

Keep out of reach of children

- If swallowed, get medical help or contact a Poison Control center right away.

Directions

- Apply generously and evenly 15 minutes before sun exposure.
- Reapply:
- after 80 minutes of swimming or sweating.
- immediately after towel drying.
- at least every 2 hours.
  - Sun Protection Measures: Spending time in the sun increases your risk of skin cancer and early skin aging. To decrease this risk, regularly use a sunscreen with a Broad Spectrum SPF value of 15 or higher and other sun protection measures including:
- Limit time in sun, especially from 10 a.m.-2 p.m.
- Wear long-sleeved shirts, pants, hats and sunglasses.
- Children under 6 months: Ask a doctor.

OTHER SAFETY INFORMATION

- Protect the product in this container from excessive heat and direct sun.

Inactive ingredients

Water (Aqua), Glycerin, Polyglyceryl-3 Distearate, Niacinamide, Aluminum Starch Octenylsuccinate, Trehalose, Stearyl Heptanoate, Silica, Aloe Barbadensis Leaf Juice, Panthenol, Squalane, Sodium Hyaluronate, Caprylyl Glycol, Ethylhexylglycerin, Cetearyl Alcohol, Palmitic Acid, Cetearyl Olivate, Stearic Acid, Sorbitan Olivate, Polyacrylate-13, Glyceryl Stearate Citrate, Polyisobutene, Dimethicone, Ethylhexyl Hydroxystearate, Polysorbate 20, Sorbitan Isostearate, Potassium Sorbate, Acrylates/Polytrimethylsiloxymethacrylate Copolymer, Triethoxycaprylylsilane, Phenoxyethanol, Citric Acid, Disodium EDTA, Sodium Benzoate

May contain: Bismuth Oxychloride (CI 77163), Iron Oxides (CI 77491, CI 77492, CI 77499) [C-00097]

Questions?

1-888-315-9814